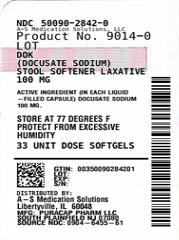 DRUG LABEL: DOK
NDC: 50090-2842 | Form: CAPSULE, LIQUID FILLED
Manufacturer: A-S Medication Solutions
Category: otc | Type: HUMAN OTC DRUG LABEL
Date: 20210301

ACTIVE INGREDIENTS: DOCUSATE SODIUM 100 mg/1 1
INACTIVE INGREDIENTS: FD&C RED NO. 40; FD&C YELLOW NO. 6; GELATIN, UNSPECIFIED; GLYCERIN; POLYETHYLENE GLYCOL, UNSPECIFIED; PROPYLENE GLYCOL; SORBITOL; WATER; ANHYDROUS CITRIC ACID

Major 44-655

Active ingredient (in each liquid-filled capsule)

Docusate sodium 100 mg

Purpose

Stool softener laxative

Uses

- relieves occasional constipation (irregularity)
- generally produces bowel movement in 12 to 72 hours

Warnings

Do not use

if you are presently taking mineral oil, unless told to do so by a doctor.

Ask a doctor before use if you have

- stomach pain
- nausea
- vomiting
- noticed a sudden change in bowel habits that lasts over 2 weeks

Stop use and ask a doctor if

- you have rectal bleeding or fail to have a bowel movement after use of a laxative. These could be signs of a serious condition.
- you need to use a laxative for more than 1 week

If pregnant or breast-feeding,

ask a health professional before use.

Keep out of reach of children.

In case of overdose, get medical help or contact a Poison Control Center (1-800-222-1222) right away.

Directions

- take with a glass of water
- take only by mouth. Doses may be taken as a single daily dose or in divided doses.

adults and children 12 years and over | take 1 to 3 capsules daily
children 2 to under 12 years | take 1 capsule daily
children under 2 years | ask a doctor

Other information

- each capsule contains: sodium 6 mg Very Low Sodium
- store at 25°C (77°F); excursions permitted between 15°-30°C (59°-86°F)
- protect from excessive humidity
- TAMPER EVIDENT: DO NOT USE IF OUTER PACKAGE IS OPENED OR BLISTER IS TORN OR BROKEN
- see end flap for expiration date and lot number

Inactive ingredients

anhydrous citric acid, edible white ink, FD&C red #40, FD&C yellow #6, gelatin, glycerin, polyethylene glycol, propylene glycol, purified water, sorbitol

Questions or comments?

(800) 616-2471

HOW SUPPLIED

Product: 50090-2842

NDC: 50090-2842-0 1 CAPSULE, LIQUID FILLED in a BLISTER PACK / 33 in a BOX, UNIT-DOSE